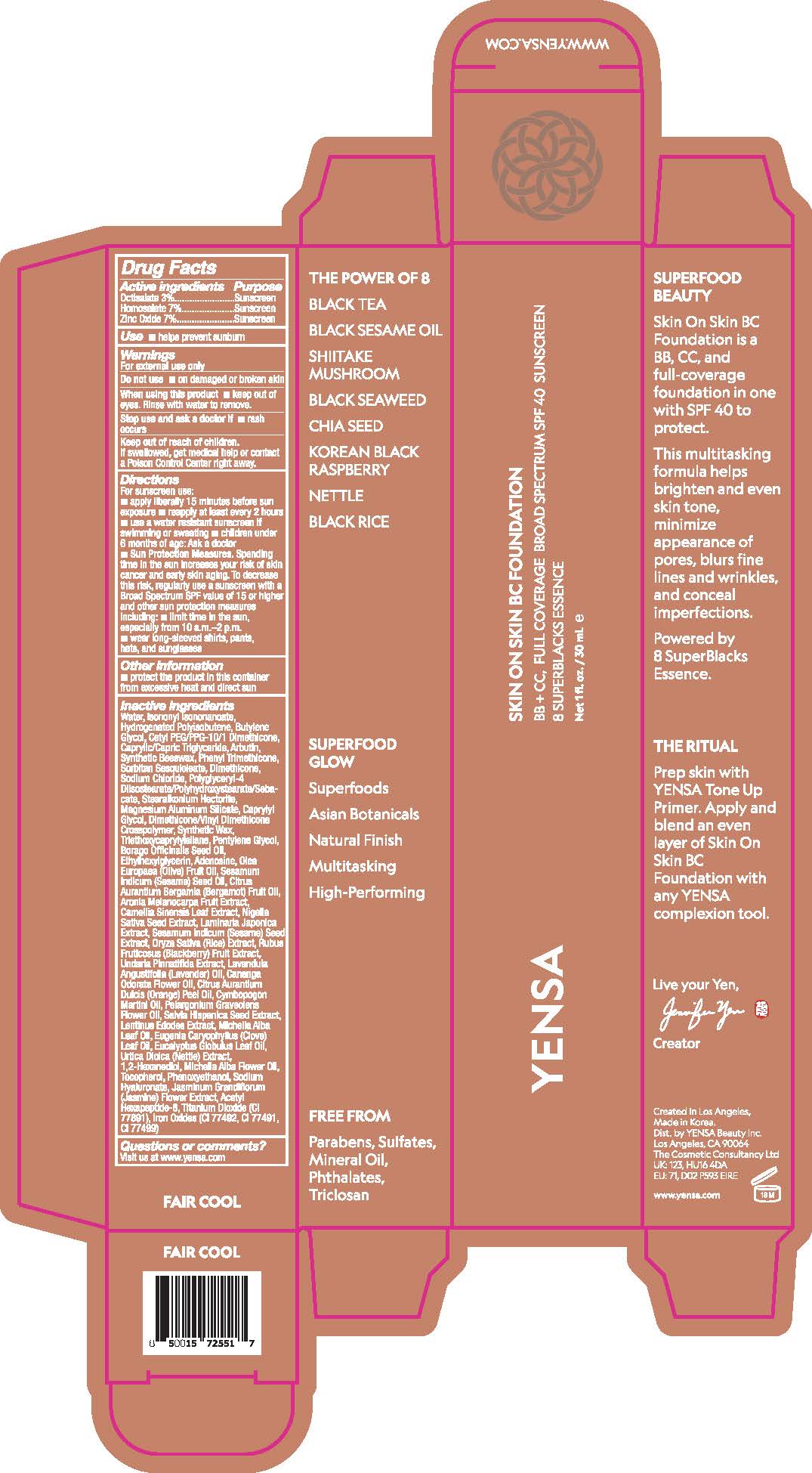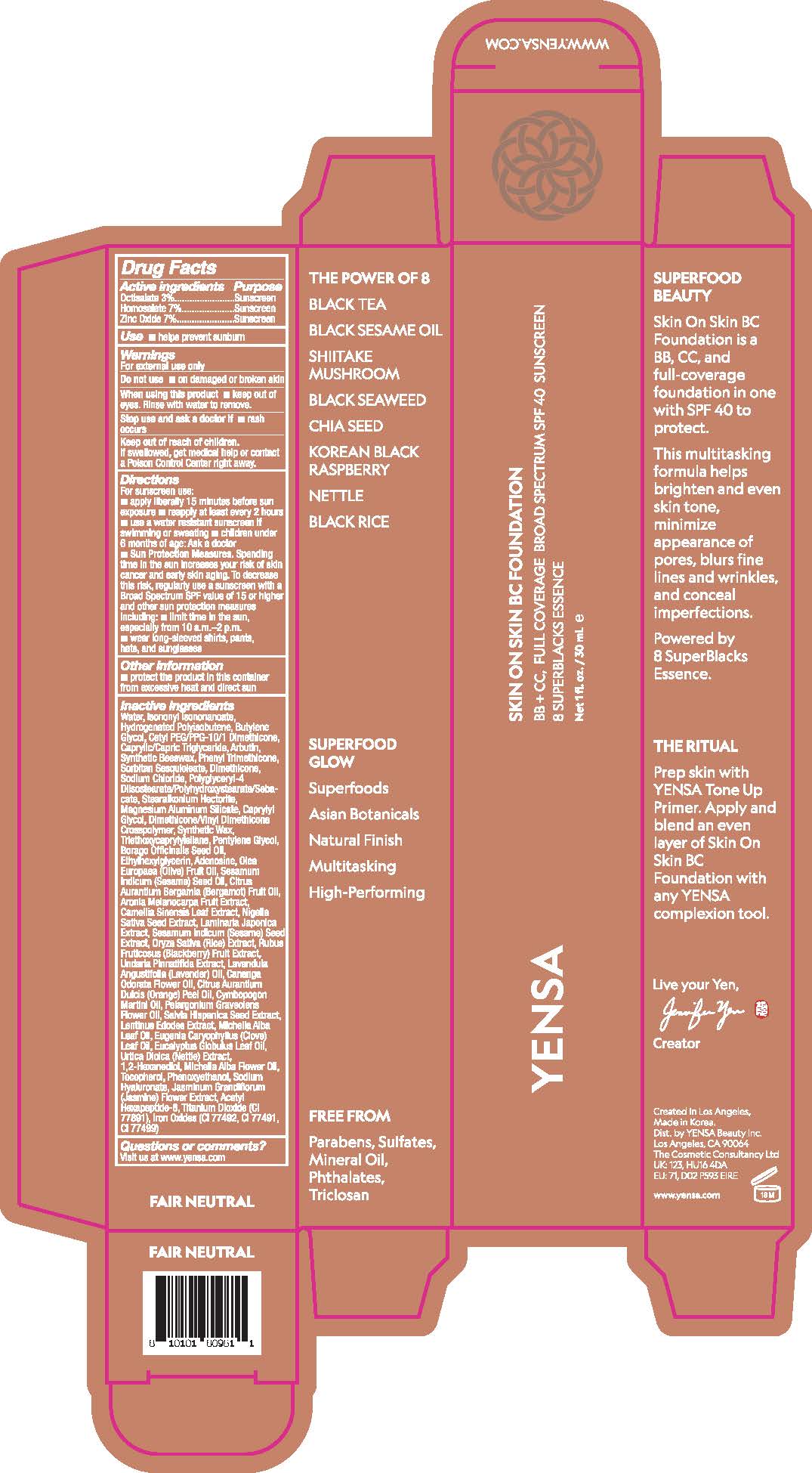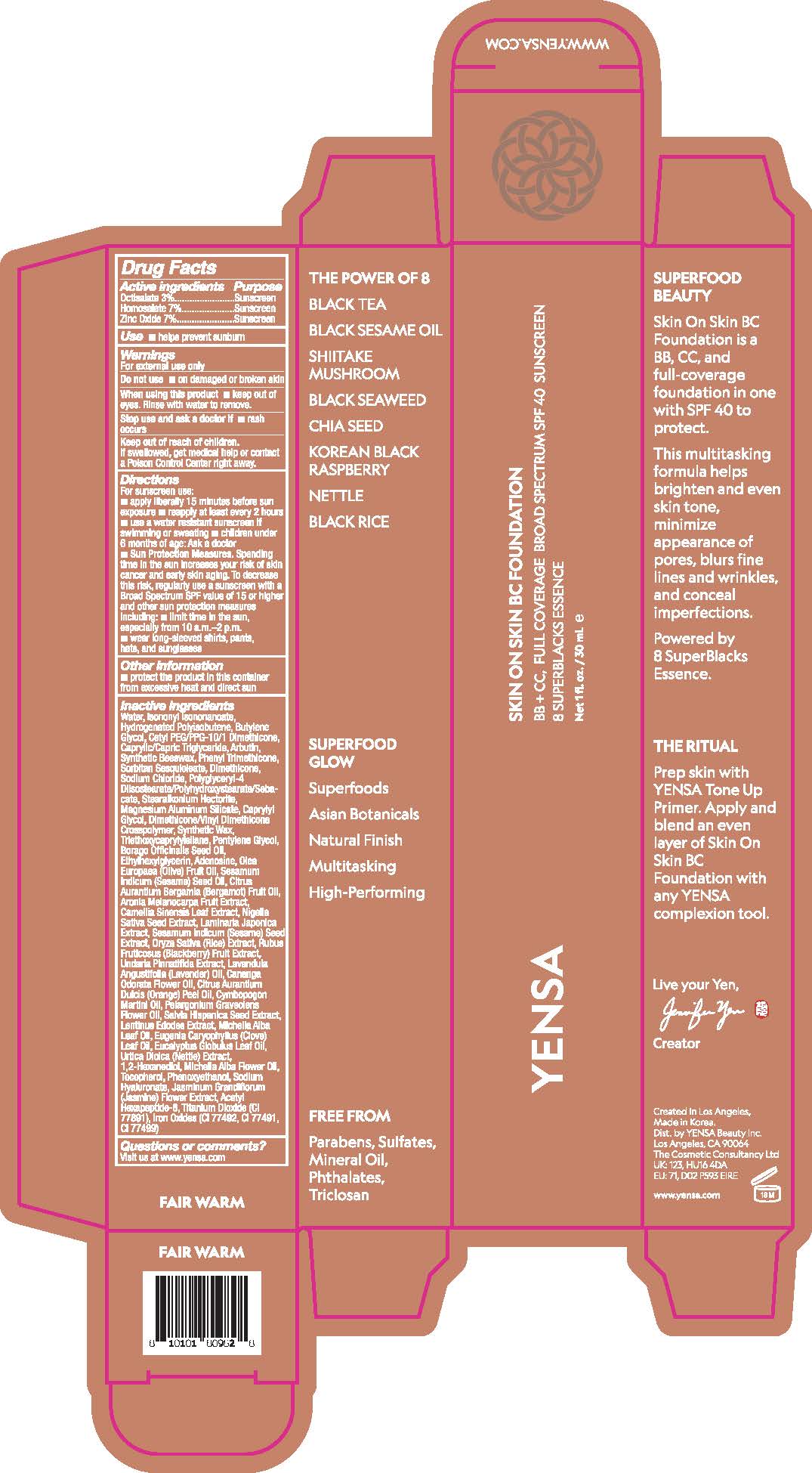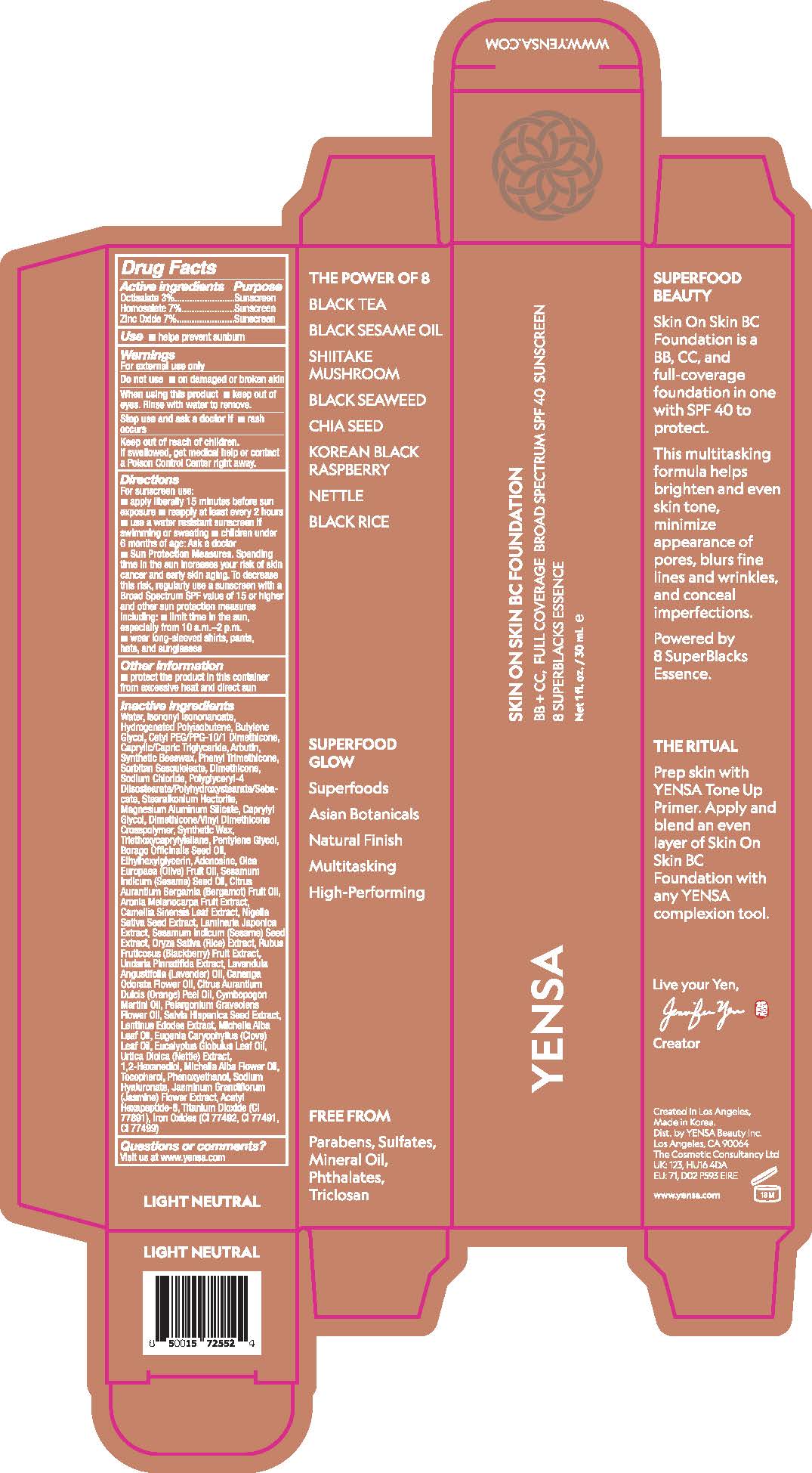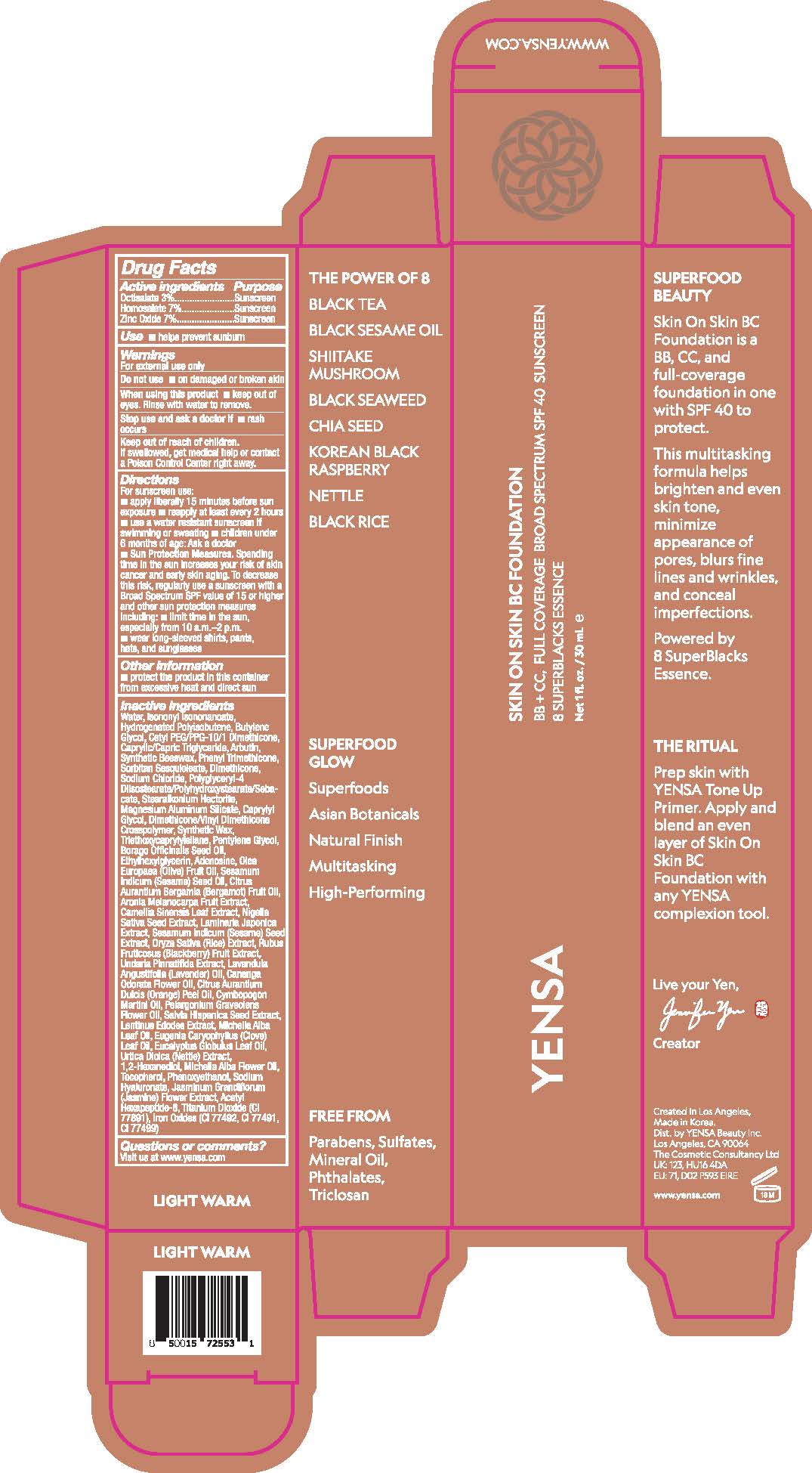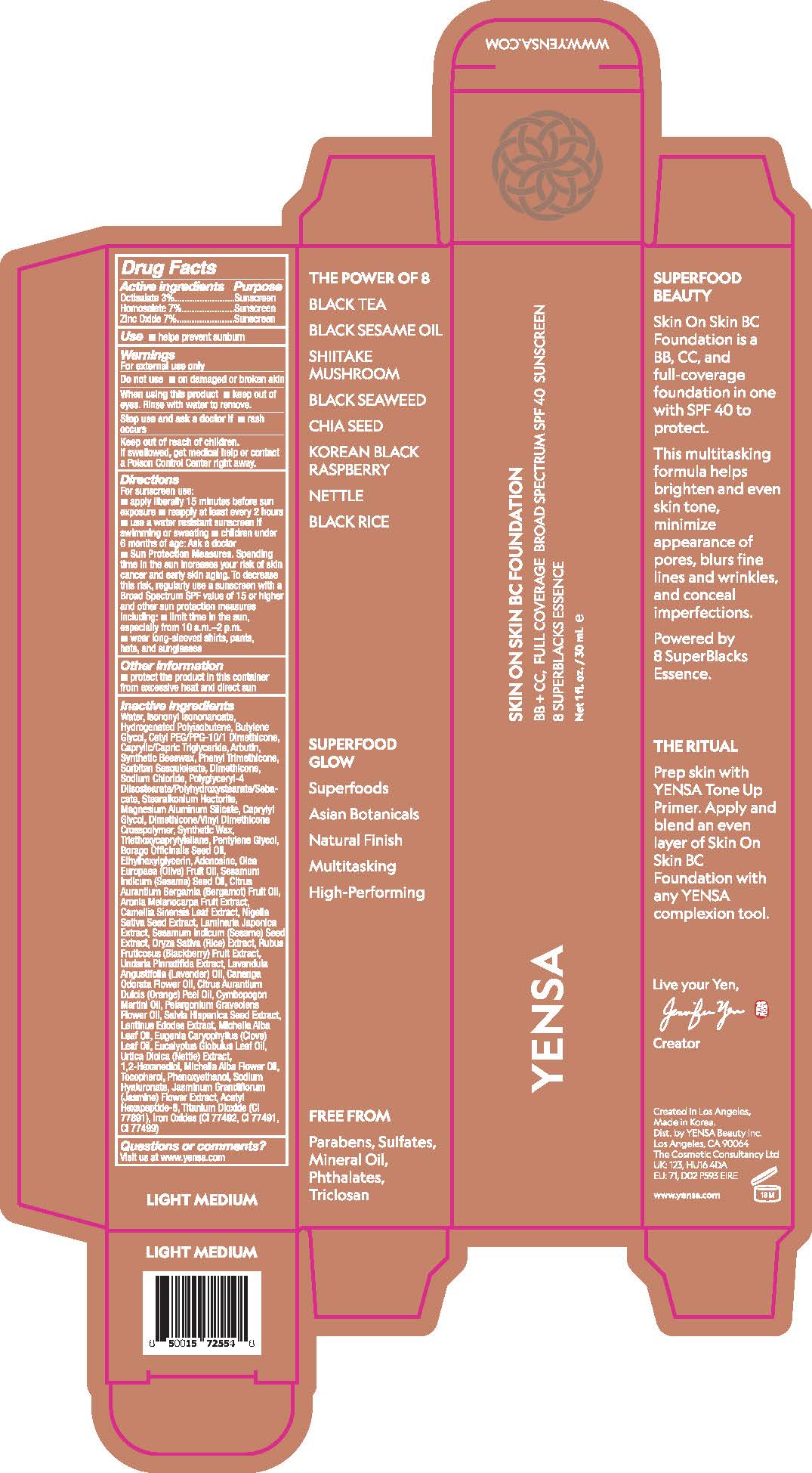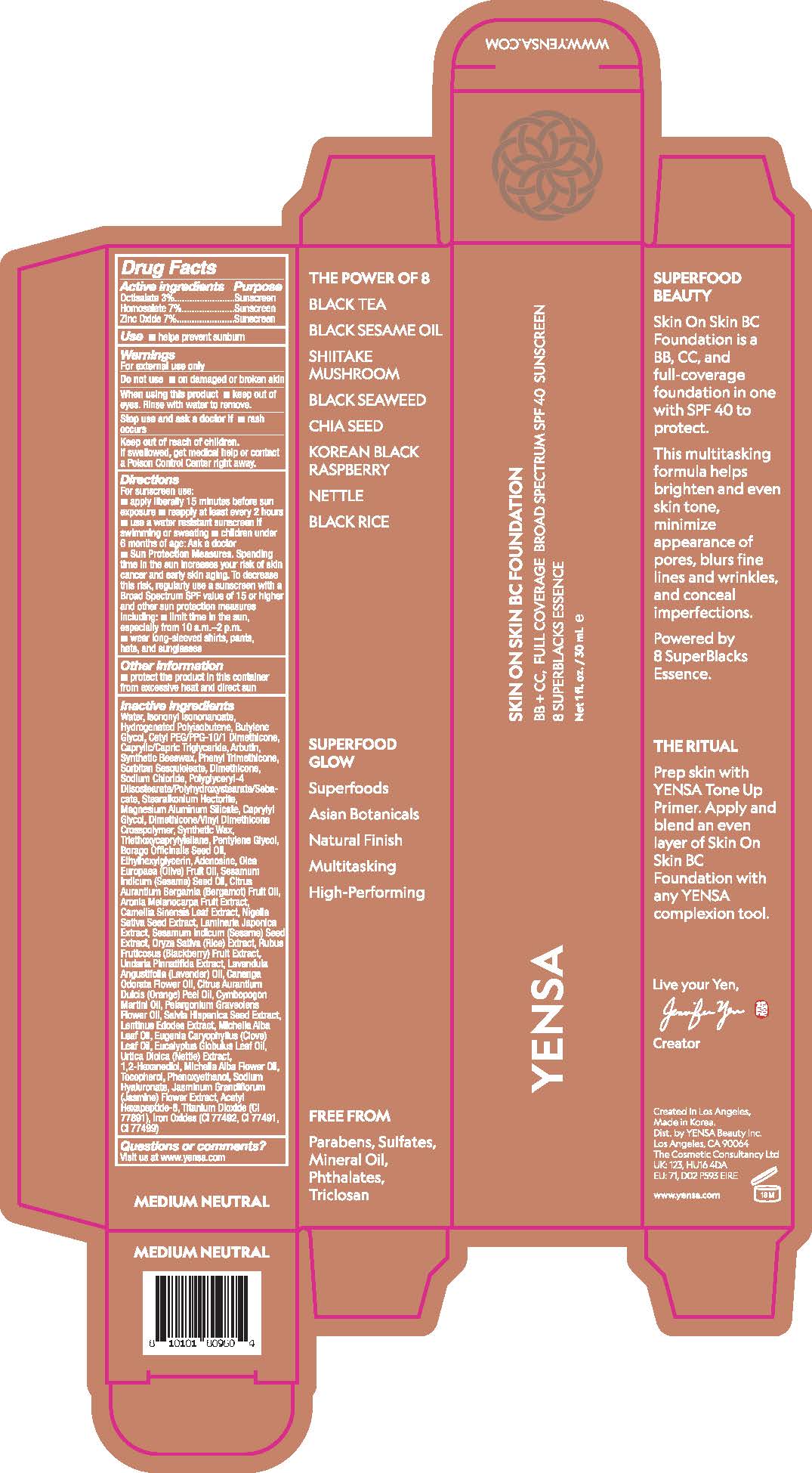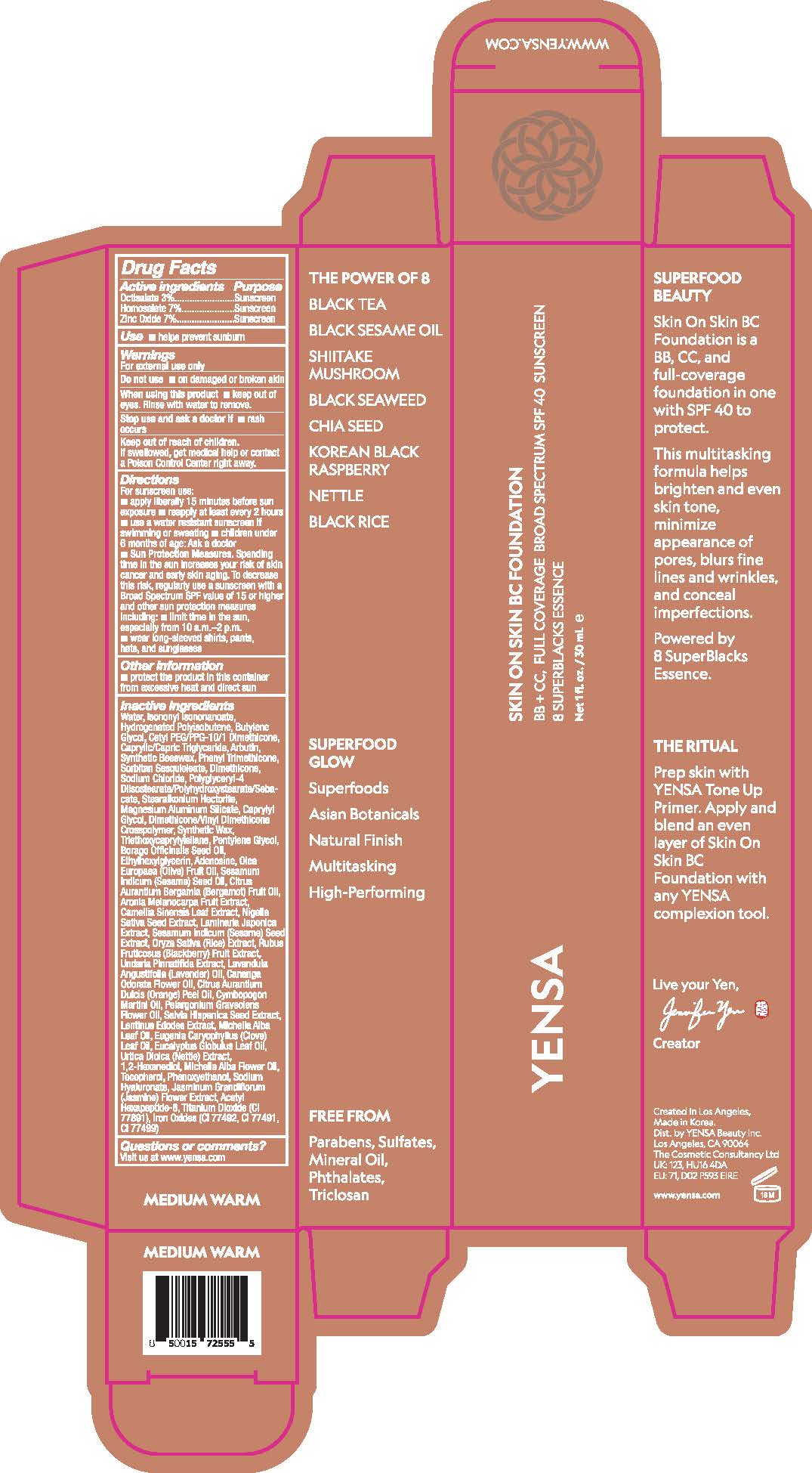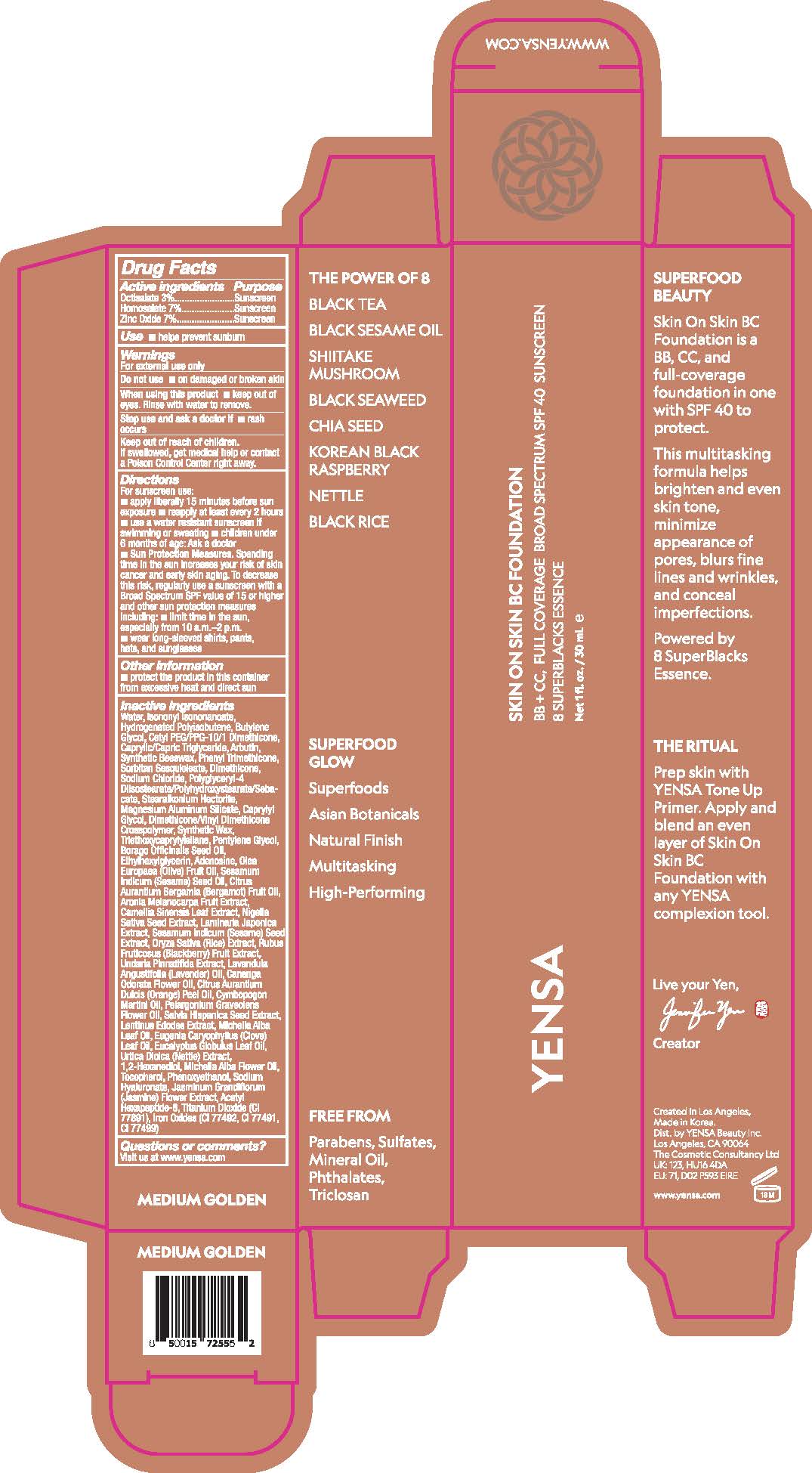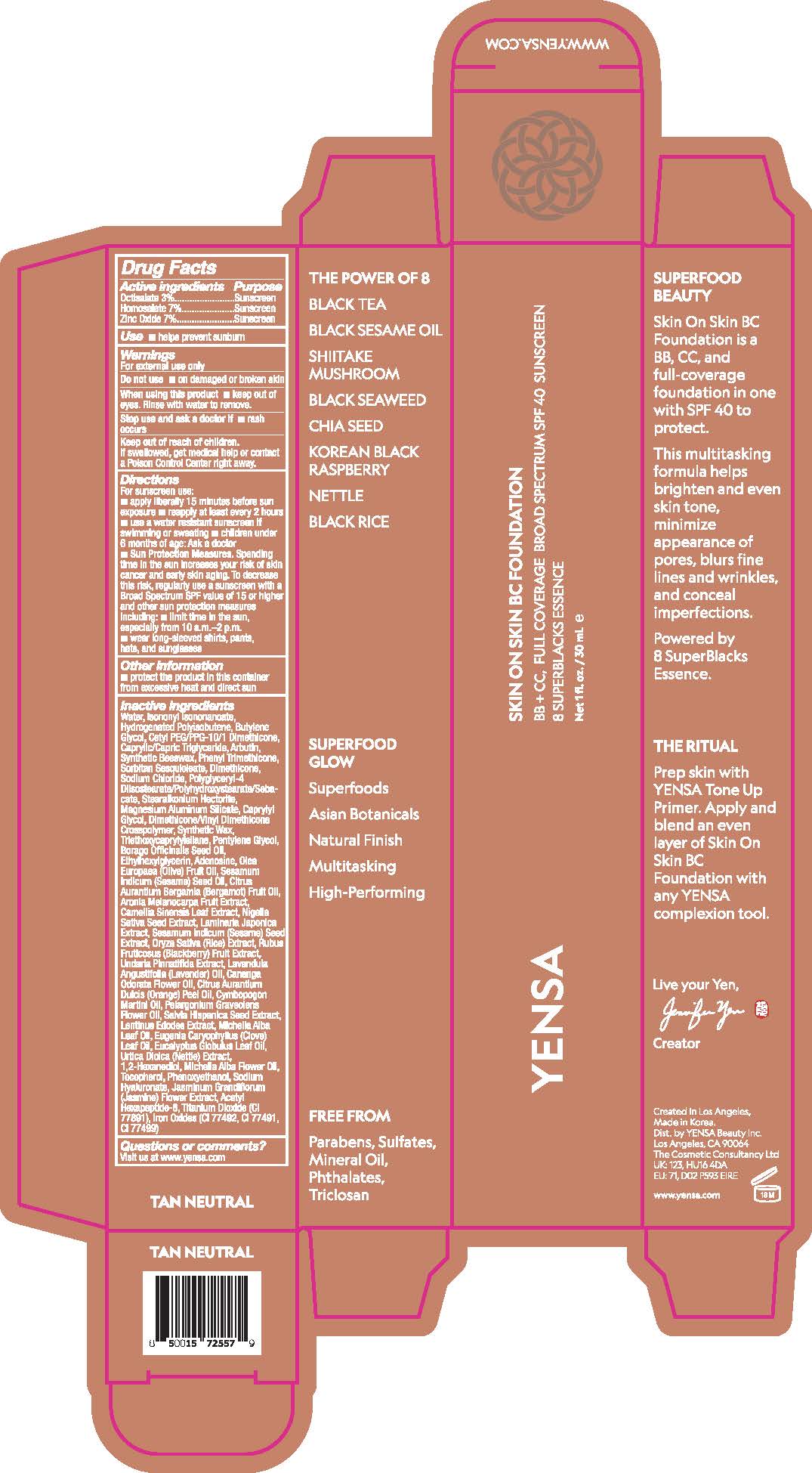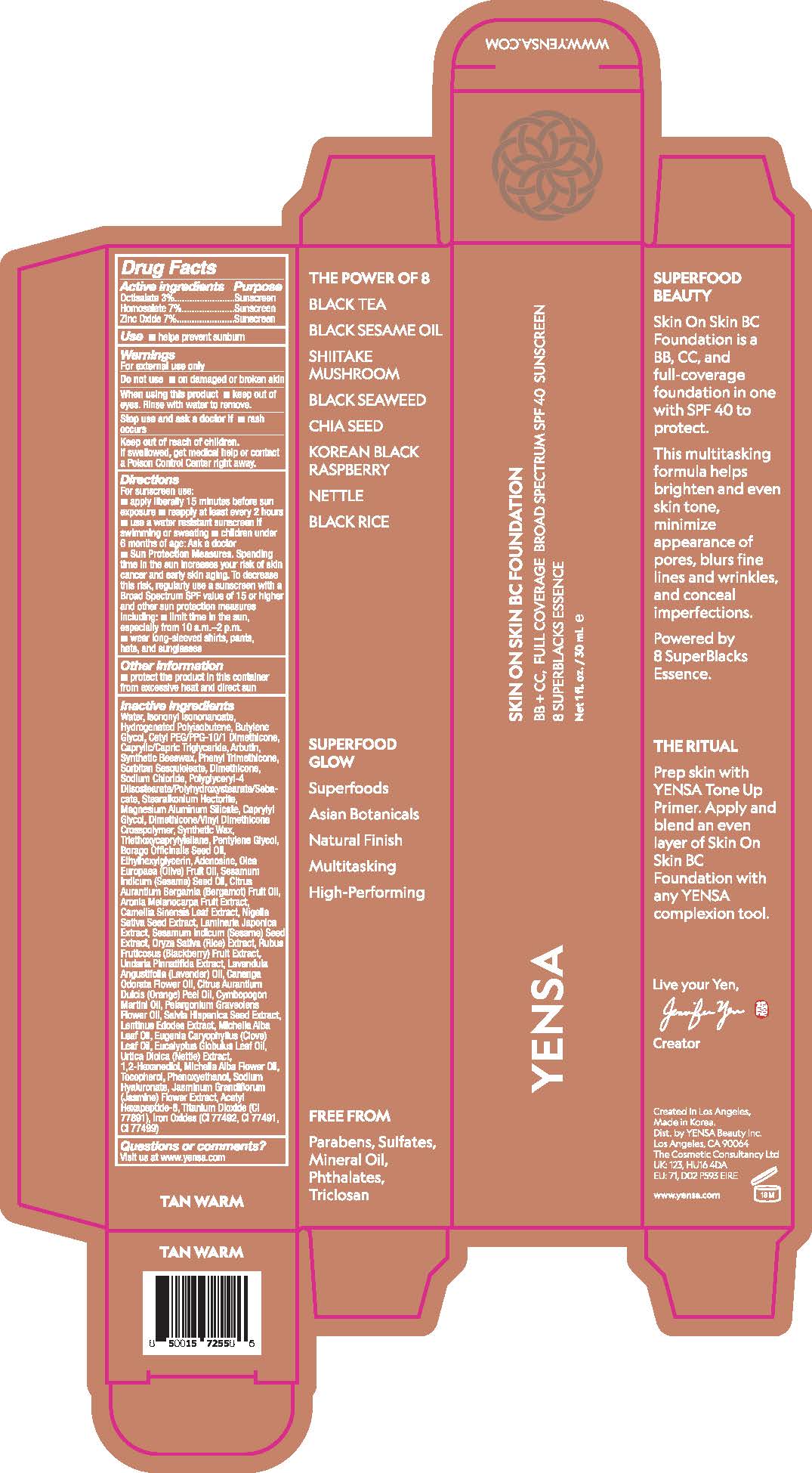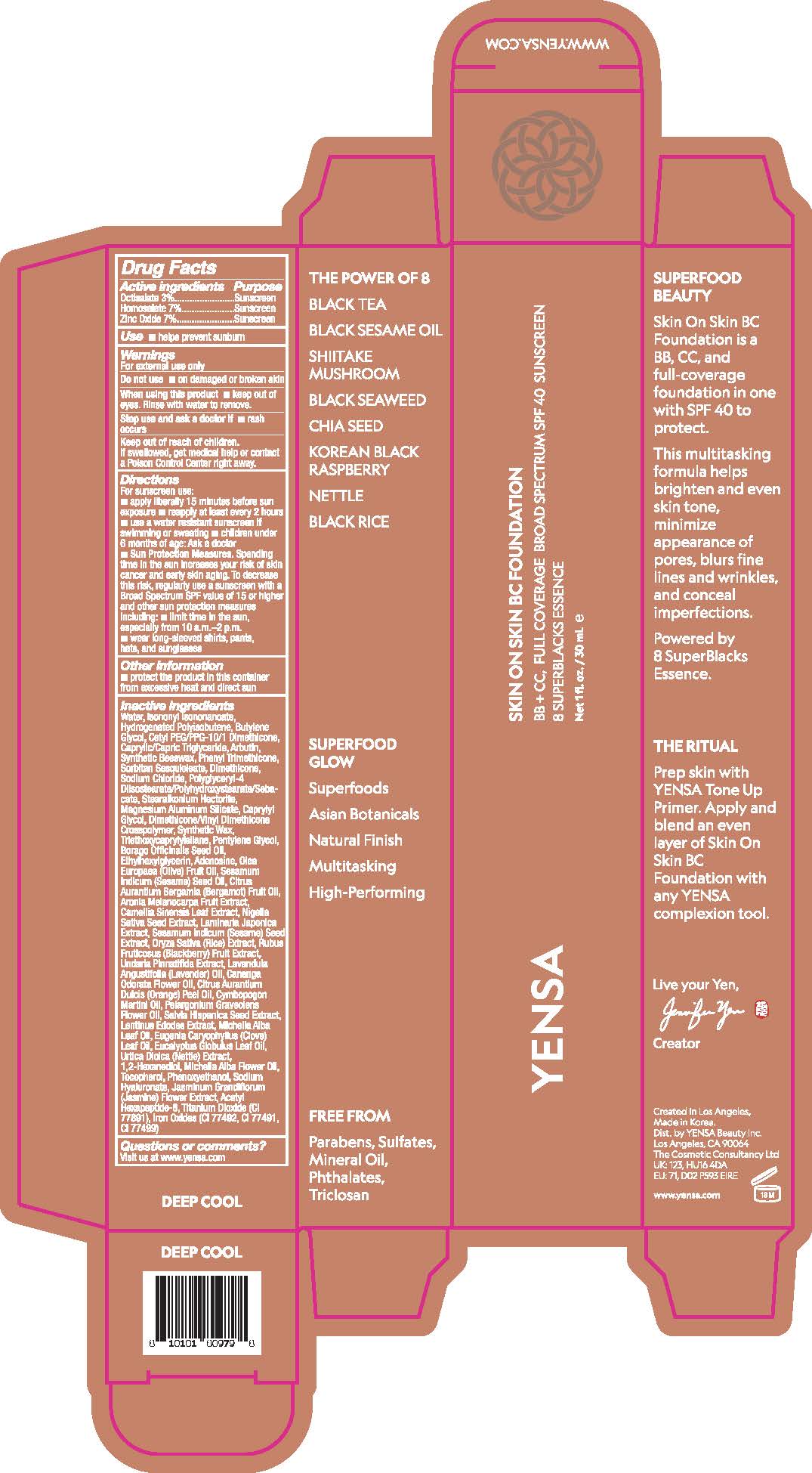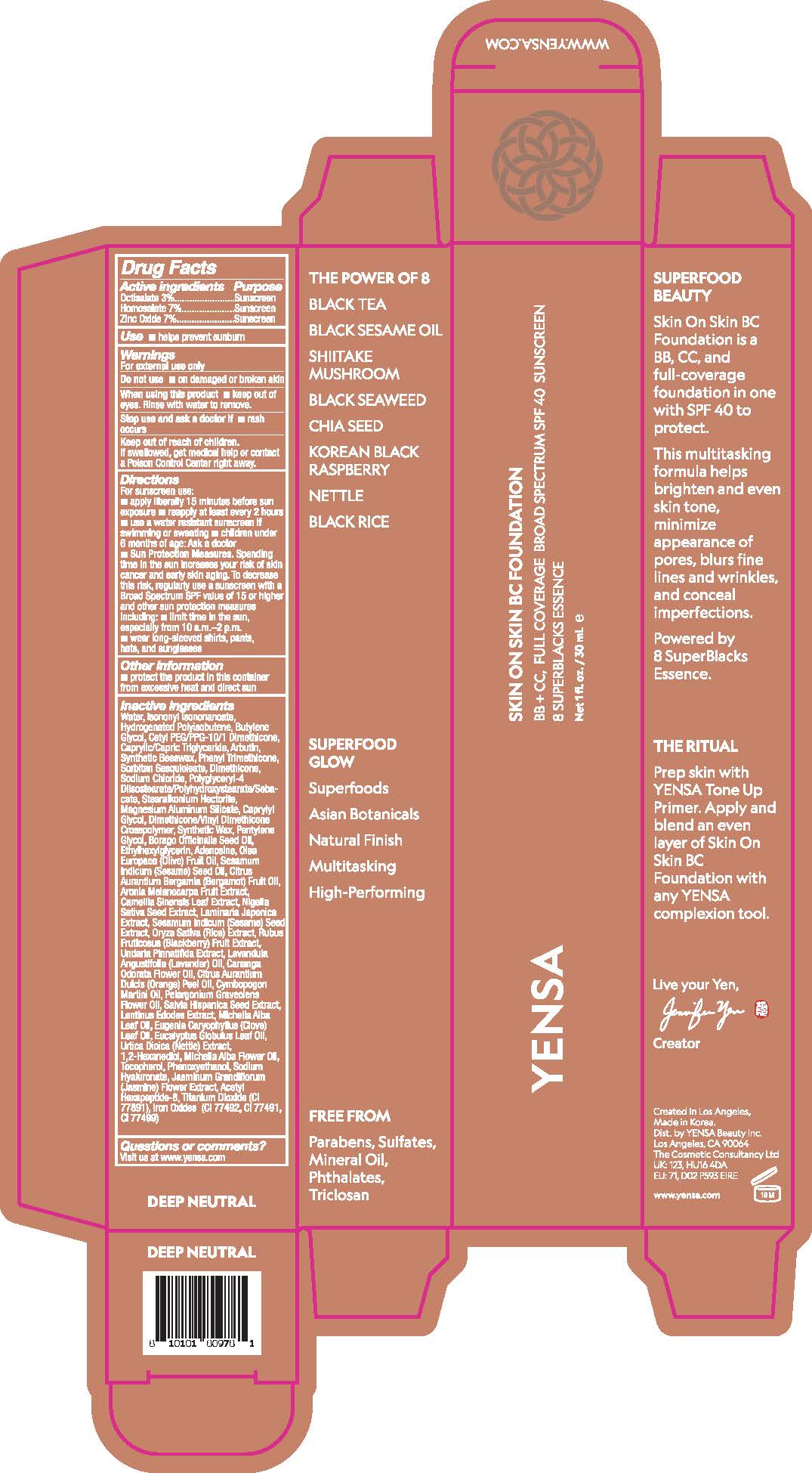 DRUG LABEL: Skin On Skin BC Foundation SPF 40 - Deep Neutral
NDC: 72782-115 | Form: CREAM
Manufacturer: YENSA Beauty, LLC
Category: otc | Type: HUMAN OTC DRUG LABEL
Date: 20251217

ACTIVE INGREDIENTS: HOMOSALATE 7 g/100 mL; OCTISALATE 3 g/100 mL; ZINC OXIDE 7 g/100 mL
INACTIVE INGREDIENTS: CHIA SEED; TOCOPHEROL; BERGAMOT OIL; GERANIOL; LINALYL ACETATE; ACETYL HEXAPEPTIDE-8; STEARALKONIUM HECTORITE; BLACKBERRY; RICE GERM; LINALOOL; LIMONENE, (+)-; MAGNESIUM ALUMINUM SILICATE; SYNTHETIC WAX (1200 MW); ARONIA MELANOCARPA FRUIT JUICE; NIGELLA SATIVA SEED; URTICA DIOICA LEAF; 1,2-HEXANEDIOL; PHENOXYETHANOL; YLANG-YLANG OIL; PELARGONIUM GRAVEOLENS FLOWER OIL; TITANIUM DIOXIDE; FERROUS OXIDE; BUTYLENE GLYCOL; SORBITAN SESQUIOLEATE; ETHYLHEXYLGLYCERIN; BORAGO OFFICINALIS SEED OIL; ADENOSINE; HYALURONATE SODIUM; WATER; ISONONYL ISONONANOATE; DIMETHICONE; TRIETHOXYCAPRYLYLSILANE; PENTYLENE GLYCOL; ORANGE OIL, COLD PRESSED; ARBUTIN; CETYL PEG/PPG-10/1 DIMETHICONE (HLB 2); CAPRYLIC/CAPRIC TRIGLYCERIDE; SYNTHETIC BEESWAX; POLYGLYCERYL-4 DIISOSTEARATE/POLYHYDROXYSTEARATE/SEBACATE; SODIUM CHLORIDE; DIMETHICONE/VINYL DIMETHICONE CROSSPOLYMER (HARD PARTICLE); SESAMUM INDICUM (SESAME) SEED OIL; SESAMUM INDICUM (SESAME) SEED; LAMINARIA JAPONICA; GREEN TEA LEAF; LENTINULA EDODES MYCELIUM; LAVENDER OIL; PINENE; EUGENIA CARYOPHYLLUS (CLOVE) LEAF OIL; BETA-CARYOPHYLLENE; UNDARIA PINNATIFIDA; HYDROGENATED POLYISOBUTENE (450 MW); PHENYL TRIMETHICONE; CAPRYLYL GLYCOL

Drug Facts

Active ingredients

Octisalate 3%

Homosalate 7%

Zinc Oxide 7%

Purpose

Sunscreen

Use

- helps prevent sunburn

Warnings

For external use only

Do not use

- on damaged or broken skin

When using this product

- keep out of eyes. Rinse with water to remove.

Stop use and ask a doctor if

- rash occurs

Keep out of reach of children.

If swallowed, get medical help or contact a Poison Control Center right away.

Directions

For sunscreen use:

- apply liberally 15 minutes before sun exposure
- reapply at least every 2 hours
- use a water resistant sunscreen if swimming or sweating
- children under 6 months of age: Ask a doctor
- Sun Protection Measures. Spending time in the sun increases your risk of skin cancer and early skin aging. To decrease this risk, regularly use a sunscreen with a Broad Spectrum SPF value of 15 or higher and other sun protection measures including:
- limit time in the sun, especially from 10 a.m.-2 p.m.
- wear long-sleeved shirts, pants, hats, and sunglasses

Other information

- protect the product in this container from excessive heat and direct sun

Inactive ingredients

Water, Isononyl Isononanoate, Hydrogenated Polyisobutene, Butylene Glycol, Cetyl PEG/PPG-10/1 Dimethicone, Caprylic/Capric Triglyceride, Arbutin, Phenyl Trimethicone, Synthetic Beeswax, Sorbitan Sesquioleate, Dimethicone, Sodium Chloride,
Polyglyceryl-4 Diisostearate/Polyhydroxystearate/Sebacate, Stearalkonium Hectorite, Magnesium Aluminum Silicate, Caprylyl Glycol, Dimethicone/Vinyl Dimethicone Crosspolymer, Synthetic Wax, Triethoxycaprylylsilane, Pentylene Glycol, Borago Officinalis Seed Oil, Ethylhexylglycerin, Adenosine, Olea Europaea (Olive) Fruit Oil, Sesamum Indicum (Sesame) Seed Oil, Citrus Aurantium Bergamia (Bergamot) Fruit Oil, Aronia Melanocarpa Fruit Extract, Camellia Sinensis Leaf Extract, Nigella Sativa Seed Extract, Laminaria Japonica Extract, Sesamum Indicum (Sesame) Seed Extract, Oryza Sativa (Rice) Extract, Rubus Fruticosus (Blackberry) Fruit Extract, Undaria Pinnatifida Extract, Lavandula Angustifolia (Lavender) Oil, Cananga Odorata Flower Oil, Citrus Aurantium Dulcis (Orange) Peel Oil, Cymbopogon Martini Oil, Pelargonium Graveolens Flower Oil, Salvia Hispanica Seed Extract, Lentinus Edodes Extract, Michelia Alba Leaf Oil, Eugenia Caryophyllus (Clove) Leaf Oil, Eucalyptus Globulus Leaf Oil, Urtica Dioica (Nettle) Extract, 1,2-Hexanediol, Michelia Alba Flower Oil, Tocopherol, Phenoxyethanol, Sodium Hyaluronate, Jasminum Grandiflorum (Jasmine) Flower Extract, Acetyl Hexapeptide-8, Titanium Dioxide, Iron Oxides

Questions or comments?

Visit us at www.yensa.com

PRINCIPAL DISPLAY PANEL - 30 ML TUBE LABEL - FAIR COOL

YENSA

SKIN ON SKIN BC FOUNDATION

BB + CC, FULL COVERAGE BROAD SPECTRUM SPF 40 SUNSCREEN

8 SUPERBLACKS ESSENCE

Net 1 fl. oz. / 30 mL ℮

PRINCIPAL DISPLAY PANEL - 30 ML TUBE LABEL - FAIR NEUTRAL

YENSA

SKIN ON SKIN BC FOUNDATION

BB + CC, FULL COVERAGE BROAD SPECTRUM SPF 40 SUNSCREEN

8 SUPERBLACKS ESSENCE

Net 1 fl. oz. / 30 mL ℮

PRINCIPAL DISPLAY PANEL - 30 ML TUBE LABEL - FAIR WARM

YENSA

SKIN ON SKIN BC FOUNDATION

BB + CC, FULL COVERAGE BROAD SPECTRUM SPF 40 SUNSCREEN

8 SUPERBLACKS ESSENCE

Net 1 fl. oz. / 30 mL ℮

PRINCIPAL DISPLAY PANEL - 30 ML TUBE LABEL - LIGHT MEDIUM

YENSA

SKIN ON SKIN BC FOUNDATION

BB + CC, FULL COVERAGE BROAD SPECTRUM SPF 40 SUNSCREEN

8 SUPERBLACKS ESSENCE

Net 1 fl. oz. / 30 mL ℮

PRINCIPAL DISPLAY PANEL - 30 ML TUBE LABEL - LIGHT NEUTRAL

YENSA

SKIN ON SKIN BC FOUNDATION

BB + CC, FULL COVERAGE BROAD SPECTRUM SPF 40 SUNSCREEN

8 SUPERBLACKS ESSENCE

Net 1 fl. oz. / 30 mL ℮

PRINCIPAL DISPLAY PANEL - 30 ML TUBE LABEL - LIGHT WARM

YENSA

SKIN ON SKIN BC FOUNDATION

BB + CC, FULL COVERAGE BROAD SPECTRUM SPF 40 SUNSCREEN

8 SUPERBLACKS ESSENCE

Net 1 fl. oz. / 30 mL ℮

PRINCIPAL DISPLAY PANEL - 30 ML TUBE LABEL - MEDIUM GOLDEN

YENSA

SKIN ON SKIN BC FOUNDATION

BB + CC, FULL COVERAGE BROAD SPECTRUM SPF 40 SUNSCREEN

8 SUPERBLACKS ESSENCE

Net 1 fl. oz. / 30 mL ℮

PRINCIPAL DISPLAY PANEL - 30 ML TUBE LABEL - MEDIUM NEUTRAL

YENSA

SKIN ON SKIN BC FOUNDATION

BB + CC, FULL COVERAGE BROAD SPECTRUM SPF 40 SUNSCREEN

8 SUPERBLACKS ESSENCE

Net 1 fl. oz. / 30 mL ℮

PRINCIPAL DISPLAY PANEL - 30 ML TUBE LABEL - TAN NEUTRAL

YENSA

SKIN ON SKIN BC FOUNDATION

BB + CC, FULL COVERAGE BROAD SPECTRUM SPF 40 SUNSCREEN

8 SUPERBLACKS ESSENCE

Net 1 fl. oz. / 30 mL ℮

PRINCIPAL DISPLAY PANEL - 30 ML TUBE LABEL - TAN WARM

YENSA

SKIN ON SKIN BC FOUNDATION

BB + CC, FULL COVERAGE BROAD SPECTRUM SPF 40 SUNSCREEN

8 SUPERBLACKS ESSENCE

Net 1 fl. oz. / 30 mL ℮

PRINCIPAL DISPLAY PANEL - 30 ML TUBE LABEL - DEEP COOL

YENSA

SKIN ON SKIN BC FOUNDATION

BB + CC, FULL COVERAGE BROAD SPECTRUM SPF 40 SUNSCREEN

8 SUPERBLACKS ESSENCE

Net 1 fl. oz. / 30 mL ℮

PRINCIPAL DISPLAY PANEL - 30 ML TUBE LABEL - DEEP NEUTRAL

YENSA

SKIN ON SKIN BC FOUNDATION

BB + CC, FULL COVERAGE BROAD SPECTRUM SPF 40 SUNSCREEN

8 SUPERBLACKS ESSENCE

Net 1 fl. oz. / 30 mL ℮